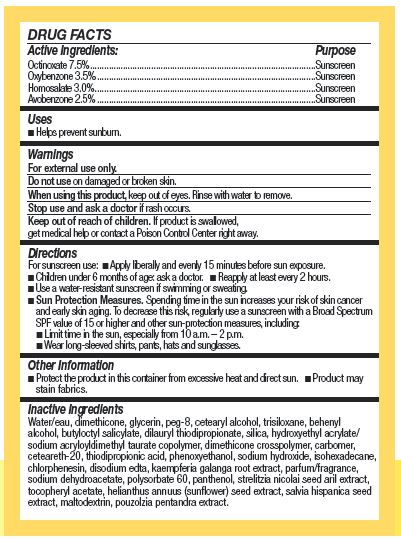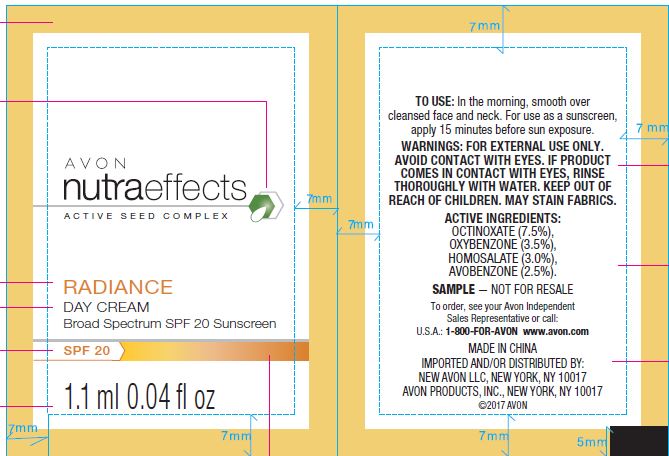 DRUG LABEL: Avon Nutra Effects
NDC: 71110-0014 | Form: CREAM
Manufacturer: Avon Products, Inc.
Category: otc | Type: HUMAN OTC DRUG LABEL
Date: 20180601

ACTIVE INGREDIENTS: OCTINOXATE 75 mg/1 g; HOMOSALATE 30 mg/1 g; AVOBENZONE 25 mg/1 g; OXYBENZONE 35 mg/1 g
INACTIVE INGREDIENTS: DILAURYL THIODIPROPIONATE; SODIUM DEHYDROACETATE; POLYSORBATE 60; WATER; GLYCERIN; ISOHEXADECANE; PANTHENOL; MALTODEXTRIN; SODIUM HYDROXIDE; DIMETHICONE; PHENOXYETHANOL; CHLORPHENESIN; THIODIPROPIONIC ACID; TRISILOXANE; BUTYLOCTYL SALICYLATE

Active Ingredients:

OCTINOXATE 7.5 % ……………………………

OXYBENZONE 3.5 % ……………………………

HOMOSALATE 3.0 % ………………………………

AVOBENZONE 2.5 % ……………………………

Purpose

............Sunscreen

............Sunscreen

............Sunscreen

............Sunscreen

Uses

Helps prevent sunburn.

Warnings

For external use only.

Do not use on damaged or broken skin.

When using this product, keep out of eyes. Rinse with water to remove.

Stop use and ask a doctor if rash occurs.

KEEP OUT OF REACH OF CHILDREN

Keep our of reach of children. If product is swallowed, get medical help or contact a Poison Control Center right away.

Directions

For suncreen use:

Apply liberally and evenly 15 minutes before sun exposure.
Children under 6 months of age: ask a doctor.
Reapply at least every 2 hours.
Use a water-resistant sunscreen if swimming or sweating.
Sun Protection Measures. Spending time in the sun increases your risk of skin cancer and early skin aging. To decrease this risk, regularly use a sunscreen with a Broad Spectrum SPF value of 15 or higher and other sun-procteion measures, including:
Limite time in the sun, expecially from 10 a.m.-2 p.m.
Wear long-sleeved shirts, pants, hats and sunglasses.

Other Information

- Protect the product in this container from excessive heat and direct sun,
- Product may stain fabrics.

Inactive ingredients

WATER/EAU, DIMETHICONE, GLYCERIN, PEG-8, CETEARYL ALCOHOL, TRISILOXANE, BEHENYL ALCOHOL, BUTYLOCTYL SALICYLATE, DILAURYL THIODIPROPIONATE, SILICA, HYDROXYETHYL ACRYLATE/SODIUM ACRYLOYLDIMETHYL TAURATE COPOLYMER, DIMETHICONE CROSSPOLYMER, CARBOMER, CETEARETH-20, THIODIPROPIONIC ACID, PHENOXYETHANOL, SODIUM HYDROXIDE, ISOHEXADECANE, CHLORPHENESIN, DISODIUM EDTA, KAEMPFERIA GALANGA ROOT EXTRACT, PARFUM/FRAGRANCE, SODIUM DEHYDROACETATE, POLYSORBATE 60, PANTHENOL, STRELITZIA NICOLAI SEED ARIL EXTRACT, TOCOPHERYL ACETATE, HELIANTHUS ANNUUS (SUNFLOWER) SEED EXTRACT, SALVIA HISPANICA SEED EXTRACT, MALTODEXTRIN, POUZOLZIA PENTANDRA EXTRACT.